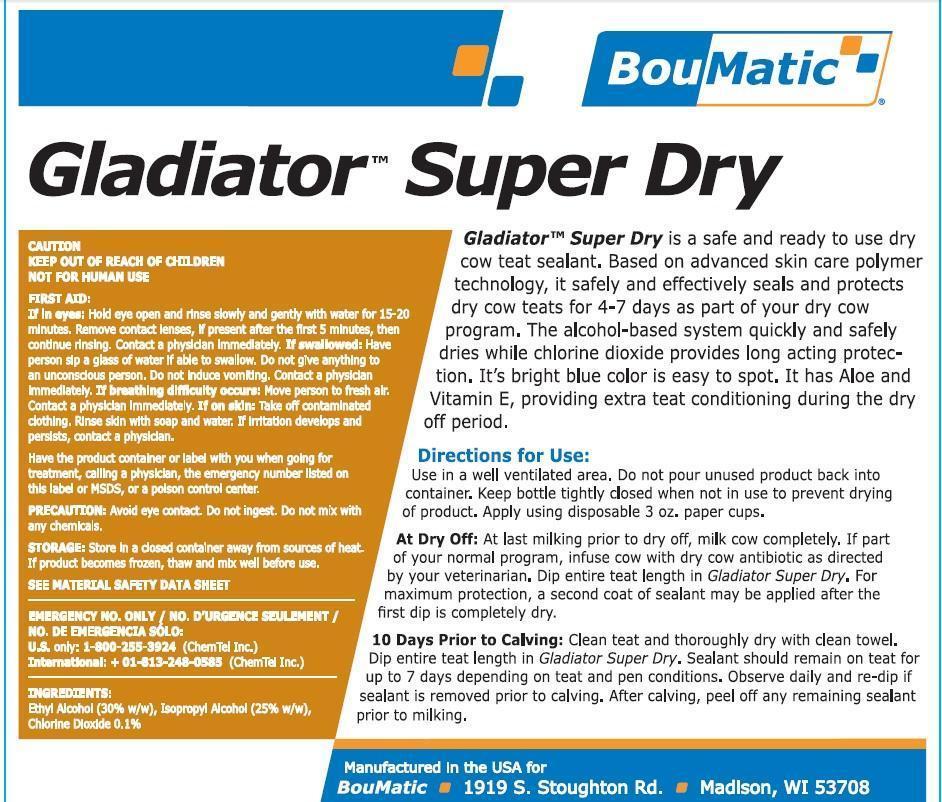 DRUG LABEL: Gladiator Super Dry
NDC: 48106-1315 | Form: LIQUID
Manufacturer: BOU-MATIC LLC
Category: animal | Type: OTC ANIMAL DRUG LABEL
Date: 20141110

ACTIVE INGREDIENTS: CHLORINE DIOXIDE 1 g/1 L

Gladiator Super Dry

INDICATIONS AND USAGE

DIRECTIONS FOR USE:

Use in a well ventilated area. Do not pour unused product back into container. Keep bottle tightly closed when not in use to prevent drying of product. Apply using disposable 3 oz. paper cups.

At Dry Off:

At last milking prior to dry off, milk cow completely. If part of your normal program, infuse cow with dry cow antibiotic as directed by your veterinarian. Dip entire teat length in Gladiator Super Dry. For maximum protection, a second coat of sealant may be applied after the first dip is completely dry.

10 Days Prior to Calving:

Clean teat and throughly dry with clean towel. Dip entire teat length in Gladiator Super Dry. Sealant should remain on teat for up to 7 days depending on teat and pen conditions. Observe daily and re-dip in sealant is removed prior to calving. After calving, peel off any remaining sealant prior to milking.

INGREDIENTS:

Ethyl Alcohol (30% w/w), Isopropyl Alcohol (25% w/w), Chlorine Dioxide 0.1%

SAFE HANDLING WARNING

CAUTION

KEEP OUT OF REACH OF CHILDREN

NOT FOR HUMAN USE

FIRST AID:
If in eyes: Hold eye open and rinse slowly and gently with water for 15-20 minutes. Remove contact lenses,
if present after the first 5 minutes, then continue rinsing. Contact a physician immediately.

If swallowed: Have person sip a glass of water if able to swallow. Do not give anything to an unconscious person. Do not
induce vomiting. Contact a physician immediately.

If breathing difficulty occurs: Move person to fresh air. Contact a physician immediately.

If on skin: Take off contaminated clothing. Rinse skin with soap and water. If irritation develops and persists, contact a physician.

Have the product container or label with you when going for treatment, calling a physician, the emergency
number listed on this label or MSDS, or a poison control center.

PRECAUTION: Avoid eye contact. Do not ingest. Do not mix with any chemicals.

STORAGE: Store in a closed container away from sources of heat. If product becomes frozen, thaw and mix
well before use.

SEE MATERIAL SAFETY DATA SHEET